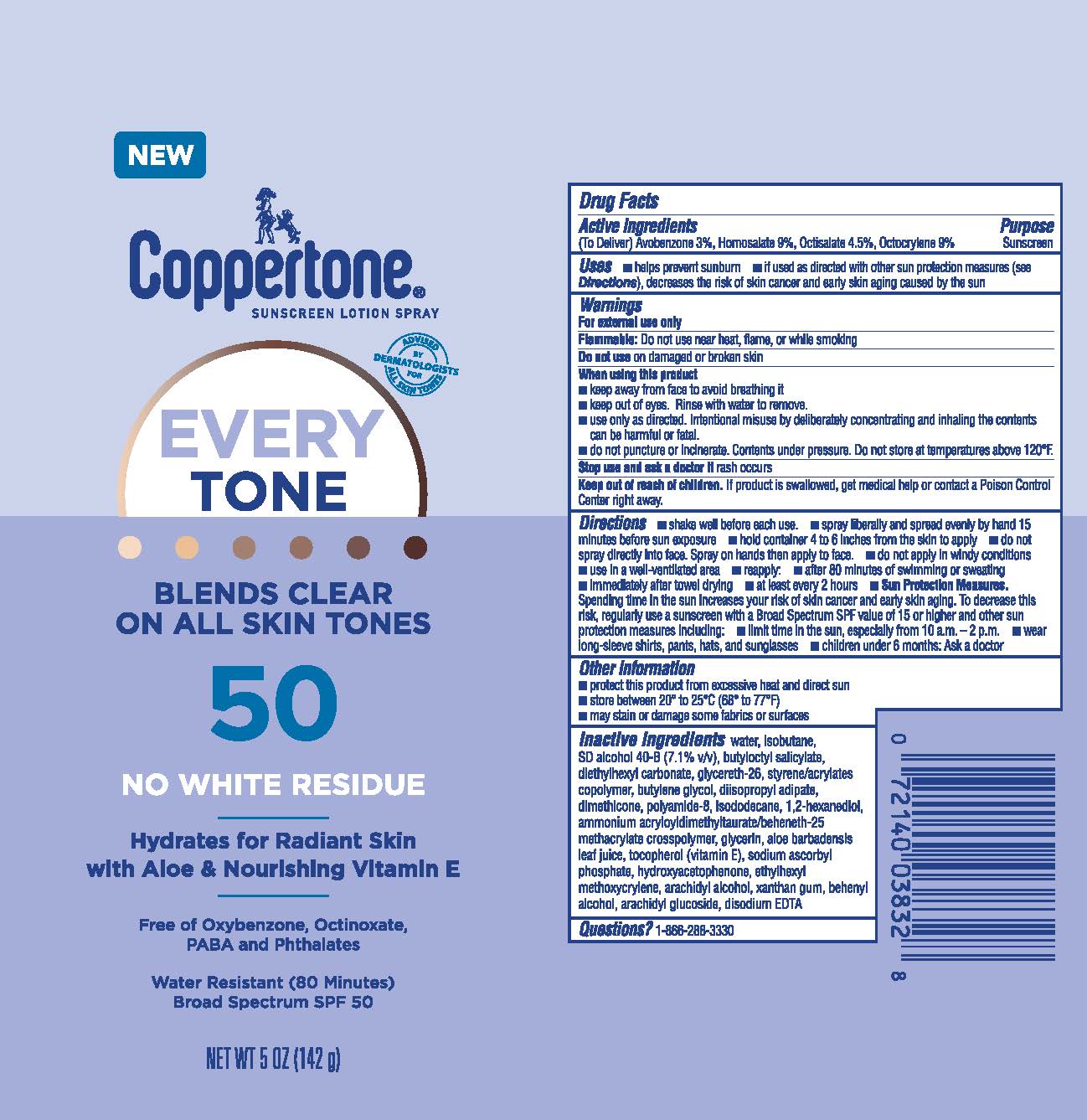 DRUG LABEL: Coppertone EveryTone Sunscreen SPF 50
NDC: 66800-5049 | Form: SPRAY
Manufacturer: Beiersdorf Inc
Category: otc | Type: HUMAN OTC DRUG LABEL
Date: 20251231

ACTIVE INGREDIENTS: OCTISALATE 4.5 g/100 g; OCTOCRYLENE 9 g/100 g; AVOBENZONE 3 g/100 g; HOMOSALATE 9 g/100 g
INACTIVE INGREDIENTS: GLYCERIN; BUTYLENE GLYCOL; DISODIUM EDTA-COPPER; POLYAMIDE-8 (4500 MW); ARACHIDYL ALCOHOL; DIISOPROPYL ADIPATE; TOCOPHEROL; XANTHAN GUM; BUTYLOCTYL SALICYLATE; GLYCERETH-26; ALOE VERA LEAF; HYDROXYACETOPHENONE; DOCOSANOL; ARACHIDYL GLUCOSIDE; WATER; SODIUM ASCORBYL PHOSPHATE; ETHYLHEXYL METHOXYCRYLENE; ALCOHOL; DIETHYLHEXYL CARBONATE; ISODODECANE; ISOBUTANE; STYRENE/ACRYLAMIDE COPOLYMER (500000 MW); DIMETHICONE; 1,2-HEXANEDIOL; AMMONIUM ACRYLOYLDIMETHYLTAURATE/BEHENETH-25 METHACRYLATE CROSSPOLYMER (52000 MPA.S)

EveryTone Lotion Spray SPF 50

Active ingredients

Avobenzone 3%, Homosalate 9%, Octisalate 4.5%, Octocrylene 9%

Purpose

Sunscreen

Use

■ helps prevent sunburn

Warnings

For external use only
Flammable:Do not use near heat, flame, or while smoking

Do not useon damaged or broken skin

When using this product
■ keep away from face to avoid breathing it

■ keep out of eyes. Rinse with water to remove.

■ use only as directed. Intentional misuse by deliberately concentrating and inhaling the contents can be harmful or fatal.

■ do not puncture or incinerate. Contents under pressure. Do not store at temperatures above 120˚F.

Stop use and ask a doctor ifrash occurs

Keep out of reach of children.If product is swallowed, get medical help or contact a Poison Control Center right away.

Directions

■ shake well before each use

■ spray liberally and spread evenly by hand 15 minutes before sun exposure

■ hold container 4 to 6 inches from the skin to apply

■ do not spray directly into face. Spray on hands then apply to face.

■ do not apply in windy conditions

■ use in a well-ventilated area

■ reapply:

■ after 80 minutes of swimming or sweating

■ immediately after towel drying

■ at least every 2 hours

■ Sun Protection Measures.Spending time in the sun increases your risk of skin cancer and early skin aging. To decrease this risk, regularly use a sunscreen with a Broad Spectrum SPF value of 15 or higher and other sun protection measures including:

■ limit time in the sun, especially from 10 a.m. – 2 p.m.

■ wear long-sleeve shirts, pants, hats, and sunglasses

■ children under 6 months: Ask a doctor

Other information

■ protect this product from excessive heat and direct sun

■ store between 20° to 25°C (68° to 77°F)

■ may stain or damage some fabrics or surfaces

Inactive ingredients

water, isobutane, SD alcohol 40-B (7.1% v/v), butyloctyl salicylate, diethylhexyl carbonate, glycereth-26, styrene/acrylates copolymer, butylene glycol, diisopropyl adipate, dimethicone, polyamide-8, isododecane, 1,2-hexanediol, ammonium acryloyldimethyltaurate/beheneth-25 methacrylate crosspolymer, glycerin, aloe barbadensis leaf juice, tocopherol (vitamin E), sodium ascorbyl phosphate, hydroxyacetophenone, ethylhexyl methoxycrylene, arachidyl alcohol, xanthan gum, behenyl alcohol, arachidyl glucoside, disodium EDTA

Questions?

1-866-288-3330

PACKAGE LABEL

Coppertone®Senscreen Lotin Spray

EveryTone

Blends Clear on All Skin Tones

50

No White Residue

Hydrates for Radiant Skin

with Aloe & Nourishing Vitamin E

Free of Oxybenzone, Octinoxate,

PABA, and Phthalates

Water Resistant (80 Minutes)

Broad Spectrum SPF 50